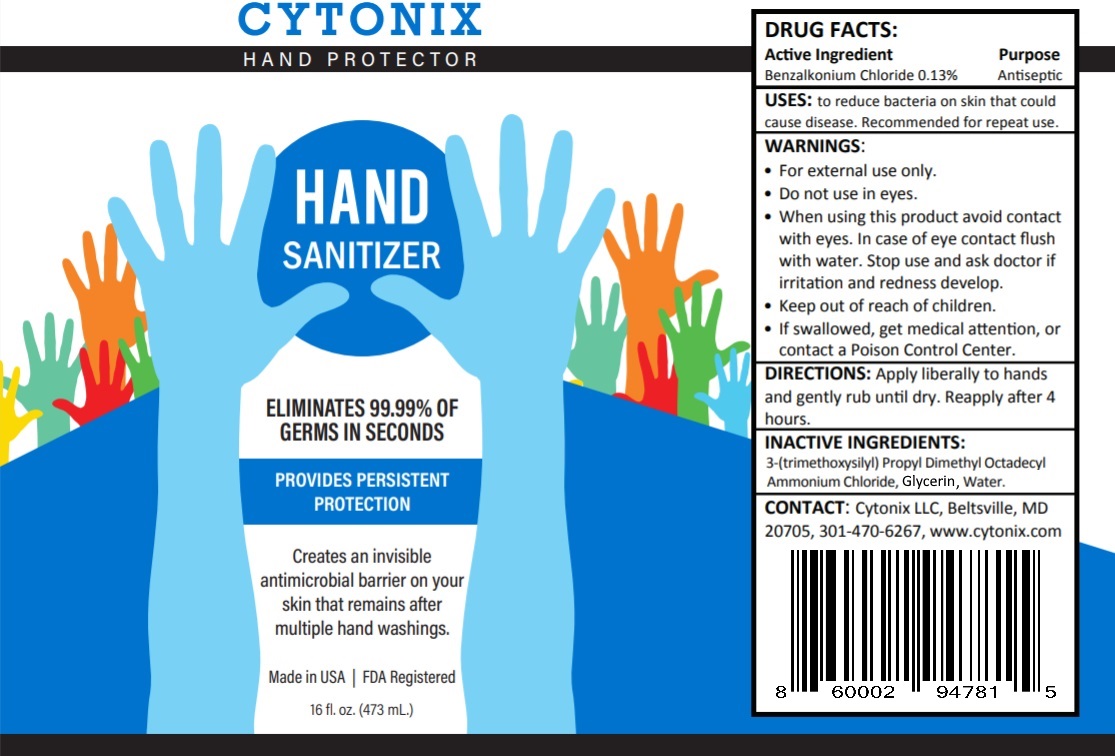 DRUG LABEL: Hand Protector
NDC: 79291-654 | Form: SOLUTION
Manufacturer: Cytonix, LLC
Category: otc | Type: HUMAN OTC DRUG LABEL
Date: 20200918

ACTIVE INGREDIENTS: BENZALKONIUM CHLORIDE 0.13 g/100 mL
INACTIVE INGREDIENTS: WATER 98 g/100 mL; GLYCERIN 1.45 g/100 mL; OCTADECYLDIMETHYL(3-TRIHYDROXYSILYLPROPYL)AMMONIUM CHLORIDE 0.5 g/100 mL

Active Ingredient. Benzalkonium Chloride 0.13%

Purpose: Antiseptic. Hand and skin sanitizer.

INDICATIONS AND USAGE

USES: to reduce bacteria on the skin that could cause disease. Recommended for repreat use.

WARNINGS:

For external use only.

Do not use in the eyes.

When using this product avoid content with eyes. In case of eye contact flush with water. Stop use and ask doctor if irritation and redness develope.

Keep out of reach of children.

If swallowed, get medical attention or contact a Poison Control Center.

Keep out of reach of children

WHEN USING

Avoid contact with eyes. In case of contact flush with plenty of water.

Stop use and ask doctor if irritation or redness develop.

INACTIVE INGREDIENT

3-(trimethoxysilyl) Propyl Dimethyl Octadecyl Ammonium Chloride, Glycerin, Water

DOSAGE AND ADMINISTRATION

Apply liberally to hands and gently rub until dry. Reapply after 4 hours.

QUESTIONS

Cytonix, LLC, Beltsville, MD

20705 USA 301-470-6267

www.cytonix.com

Hand Protector Label 79291-654-01 473mL